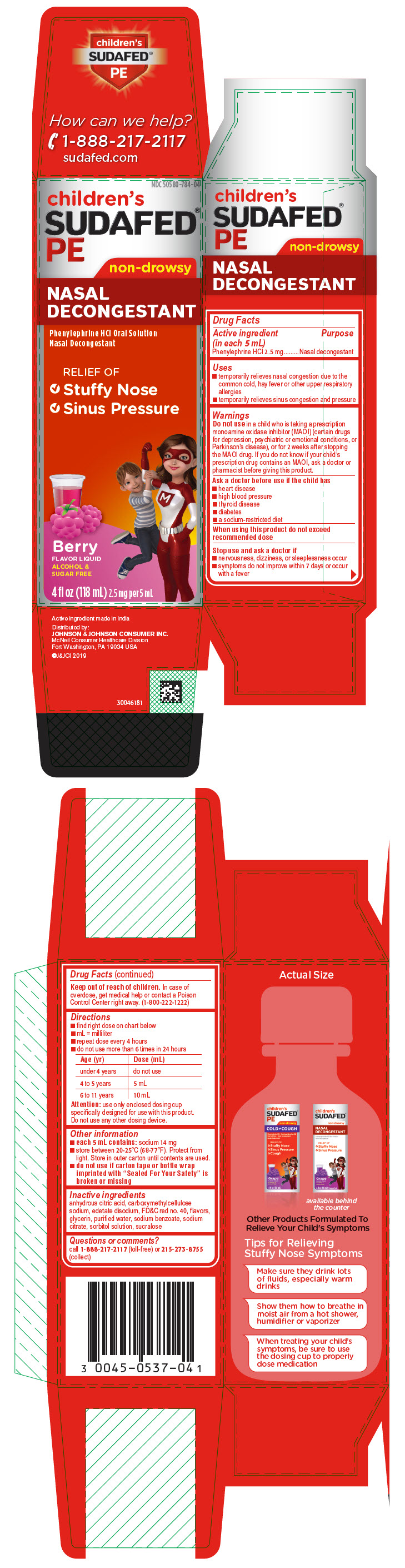 DRUG LABEL: Childrens Sudafed PE
NDC: 50580-784 | Form: SOLUTION
Manufacturer: Kenvue Brands LLC
Category: otc | Type: HUMAN OTC DRUG LABEL
Date: 20241104

ACTIVE INGREDIENTS: PHENYLEPHRINE HYDROCHLORIDE 2.5 mg/5 mL
INACTIVE INGREDIENTS: SODIUM CITRATE, UNSPECIFIED FORM; SORBITOL SOLUTION; SODIUM BENZOATE; SUCRALOSE; ANHYDROUS CITRIC ACID; CARBOXYMETHYLCELLULOSE SODIUM, UNSPECIFIED; EDETATE DISODIUM; FD&C RED NO. 40; GLYCERIN; WATER

Childrens Sudafed PE
NASAL DECONGESTANT

Drug Facts

Active ingredient (in each 5 mL)

Phenylephrine HCl 2.5 mg

Purpose

Nasal decongestant

Uses

- temporarily relieves nasal congestion due to the common cold, hay fever or other upper respiratory allergies
- temporarily relieves sinus congestion and pressure

Warnings

Do not use in a child who is taking a prescription monoamine oxidase inhibitor (MAOI) (certain drugs for depression, psychiatric or emotional conditions, or Parkinson's disease), or for 2 weeks after stopping the MAOI drug. If you do not know if your child's prescription drug contains an MAOI, ask a doctor or pharmacist before giving this product.

Ask a doctor before use if the child has

- heart disease
- high blood pressure
- thyroid disease
- diabetes
- a sodium-restricted diet

When using this product do not exceed recommended dose

Stop use and ask a doctor if

- nervousness, dizziness, or sleeplessness occur
- symptoms do not improve within 7 days or occur with a fever

Keep out of reach of children. In case of overdose, get medical help or contact a Poison Control Center right away. (1-800-222-1222)

Directions

- find right dose on chart below
- mL = milliliter
- repeat dose every 4 hours
- do not use more than 6 times in 24 hours

Age (yr) | Dose (mL)
under 4 years | do not use
4 to 5 years | 5 mL
6 to 11 years | 10 mL

Attention: use only enclosed dosing cup specifically designed for use with this product. Do not use any other dosing device.

Other information

- each 5 mL contains: sodium 14 mg
- store between 20-25°C (68-77°F). Protect from light. Store in outer carton until contents are used.
- do not use if carton tape or bottle wrap imprinted with "Sealed For Your Safety" is broken or missing

Inactive ingredients

anhydrous citric acid, carboxymethylcellulose sodium, edetate disodium, FD&C red no. 40, flavors, glycerin, purified water, sodium benzoate, sodium citrate, sorbitol solution, sucralose

Questions or comments?

call 1-888-217-2117 (toll-free) or 215-273-8755 (collect)

PRINCIPAL DISPLAY PANEL

NDC 50580-784-04

children's
SUDAFED®
PE

non-drowsy

NASAL
DECONGESTANT

Phenylephrine HCl Oral Solution
Nasal Decongestant

RELIEF OF

- Stuffy Nose
- Sinus Pressure

Berry
FLAVOR LIQUID
ALCOHOL &
SUGAR FREE

4 fl oz (118 mL) 2.5 mg per 5 mL